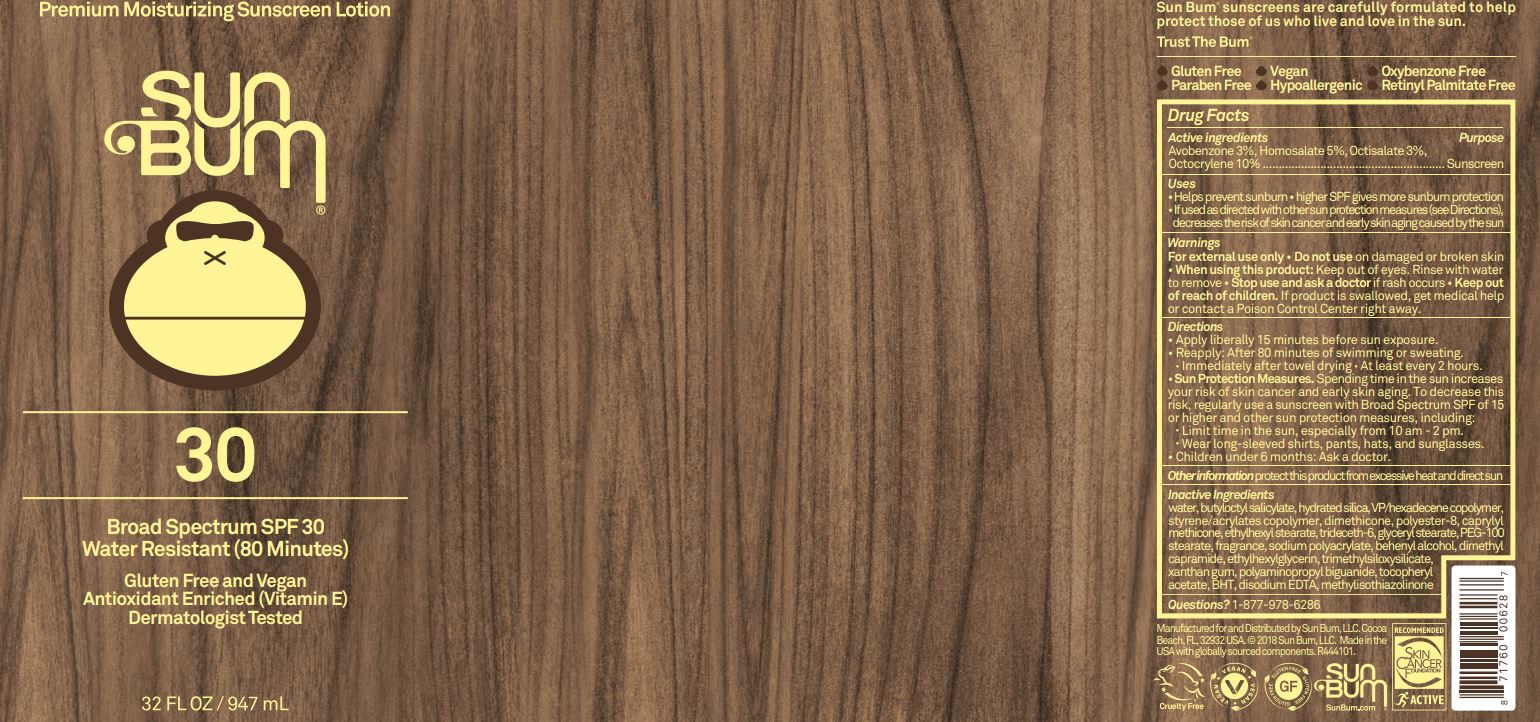 DRUG LABEL: Sun Bum SPF 30 Premium Moisturizing Sunscreen
NDC: 69039-229 | Form: LOTION
Manufacturer: Sun Bum LLC
Category: otc | Type: HUMAN OTC DRUG LABEL
Date: 20220215

ACTIVE INGREDIENTS: AVOBENZONE 30 mg/1 mL; HOMOSALATE 50 mg/1 mL; OCTISALATE 30 mg/1 mL; OCTOCRYLENE 100 mg/1 mL
INACTIVE INGREDIENTS: DIMETHYL CAPRAMIDE; ETHYLHEXYLGLYCERIN; XANTHAN GUM; .ALPHA.-TOCOPHEROL ACETATE; WATER; BUTYLOCTYL SALICYLATE; HYDRATED SILICA; VINYLPYRROLIDONE/HEXADECENE COPOLYMER; DIMETHICONE; POLYESTER-8 (1400 MW, CYANODIPHENYLPROPENOYL CAPPED); CAPRYLYL TRISILOXANE; ETHYLHEXYL STEARATE; TRIDECETH-6; GLYCERYL MONOSTEARATE; PEG-100 STEARATE; DOCOSANOL; BUTYLATED HYDROXYTOLUENE; EDETATE DISODIUM ANHYDROUS; METHYLISOTHIAZOLINONE

Sun Bum SPF 30 Premium Moisturizing Sunscreen

Active Ingredients

Avobenzone 3%, Homosalate 5%, Octisalate 3%, Octocrylene 10%

Purpose

Sunscreen

Uses

- helps prevent sunburn.
- higher SPF gives more sunburn protection
- If used as directed with other sun protection measures (see Directions), decreases the risk of skin cancer and early skin aging caused by the sun.

Warnings

For external use only.

Do not use

on damaged or broken skin.

When using this product:

Keep out of eyes. Rinse with water to remove.

Stop use and ask a doctor

if rash occurs.

Keep out of reach of children.

If product is swallowed, get medical help or contact a Poison Control Center right away.

Directions

- Apply liberally 15 minutes before sun exposure.
- Reapply: After 80 minutes of swimming or sweating.
- Immediately after towel drying
- At least every 2 hours.
- Sun Protection Measures. Spending time in the sun increases your risk of skin cancer and early skin aging. To decrease this risk, regularly use a sunscreen with Broad Spectrum SPF of 15 or higher and other sun protection measures, including:
- Limit time in the sun, especially from 10 am - 2 pm.
- Wear long-sleeved shirts, pants, hats, and sunglasses.
- Children under 6 months: Ask a doctor.

Other Information

protect this product from excessive heat and directed sun

Inactive ingredients

water, butyloctyl salicylate, hydrated silica, VP/hexadecene copolymer, styrene/acrylates copolymer, dimethicone, polyester-8, caprylyl methicone, ethylhexyl stearate, trideceth-6, glyceryl stearate, PEG-100 stearate, fragrance, sodium polyacrylate, behenyl alcohol, dimethyl capramide, ethylhexylglycerin, trimethylsloxysilicate, xanthan gum, polyaminopropyl biguanide, tocopheryl acetate, BHT, disodium EDTA, methylisothiazolinone

Questions?

Call 1-877-978-6286